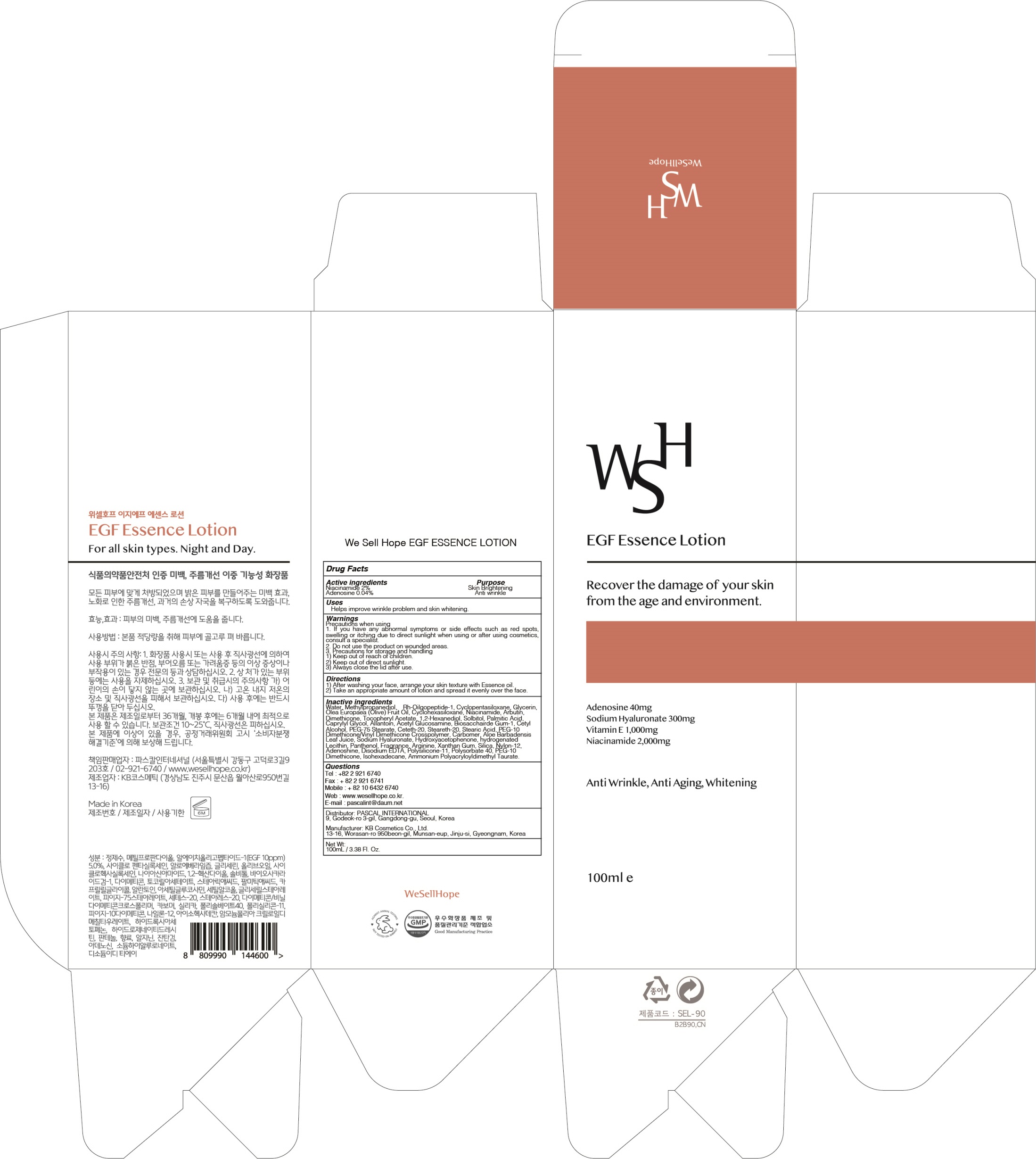 DRUG LABEL: We Sell Hope EGF ESSENCE
NDC: 73735-010 | Form: LOTION
Manufacturer: PASCAL INTERNATIONAL
Category: otc | Type: HUMAN OTC DRUG LABEL
Date: 20200603

ACTIVE INGREDIENTS: Niacinamide 2.0 g/100 mL; Adenosine 0.04 g/100 mL
INACTIVE INGREDIENTS: Water; Methylpropanediol

ACTIVE INGREDIENT

Active ingredients: Niacinamide 2%, Adenosine 0.04%

INACTIVE INGREDIENT

Inactive ingredients:
Water, Methylpropanediol, Cyclopentasiloxane, Glycerin, Olea Europaea (Olive) Fruit Oil, Cyclohexasiloxane, Arbutin, Dimethicone, Tocopheryl Acetate, 1,2-Hexanediol, Solbitol, Palmitic Acid, Caprylyl Glycol, Allantoin, Acetyl Glucosamine, Biosacchairde Gum-1, Cetyl Alcohol, PEG-75 Stearate, Ceteth-20, Steareth-20, Stearic Acid, PEG-10 Dimethicone/Vinyl Dimethicone Crosspolymer, Carbomer, Aloe Barbadensis Leaf Juice, Sodium Hyaluronate, Hydroxyacetophenone, hydrogenated Lecithin, Panthenol, Fragrance, Arginine, Xanthan Gum, Silica, Nylon-12, Adenoshine, Disodium EDTA, Polysilicone-11, Polysorbate 40, PEG-10 Dimethicone, Isohexadecane, Ammonium Polyacryloyldimethyl Taurate, rh-Oilgopeptide-1

PURPOSE

Purpose: Skin Brightening, Anti wrinkle

WARNINGS

Precautions when using
1. If you have any abnormal symptoms or side effects such as red spots, swelling or itching due to direct sunlight when using or after using cosmetics, consult a specialist.
2. Do not use the product on wounded areas.
3. Precautions for storage and handling
1) Keep out of reach of children.
2) Keep out of direct sunlight.
3) Always close the lid after use.

KEEP OUT OF REACH OF CHILDREN

Uses

Helps improve wrinkle problem and skin whitening.

Directions

1) After washing your face, arrange your skin texture with Essence oil.
2) Take an appropriate amount of lotion and spread it evenly over the face.

QUESTIONS

Tel : +82 2 921 6740
Fax : + 82 2 921 6741
Mobile : + 82 10 6432 6740
Web : www.wesellhope.co.kr.
E-mail : pascalint@daum.net